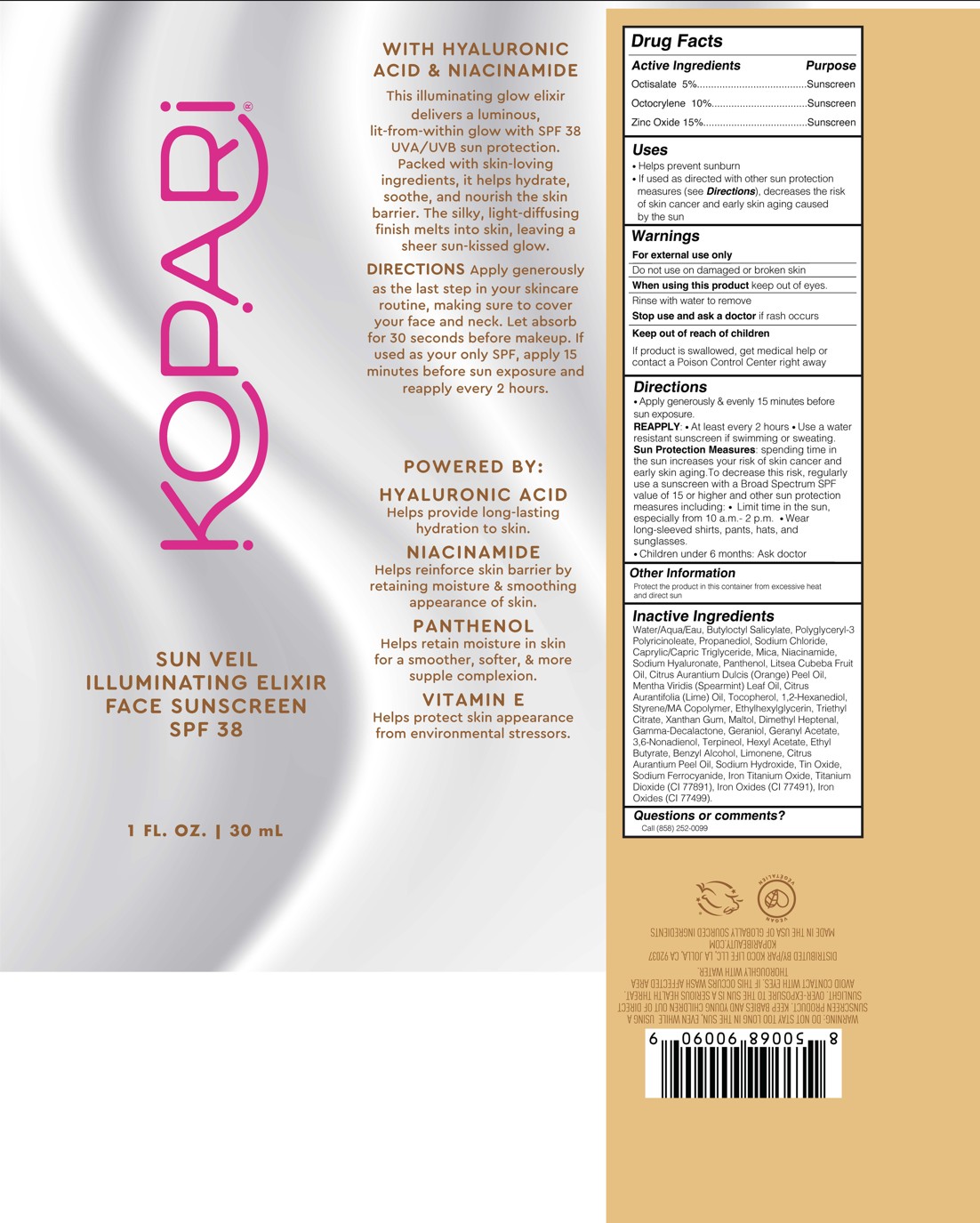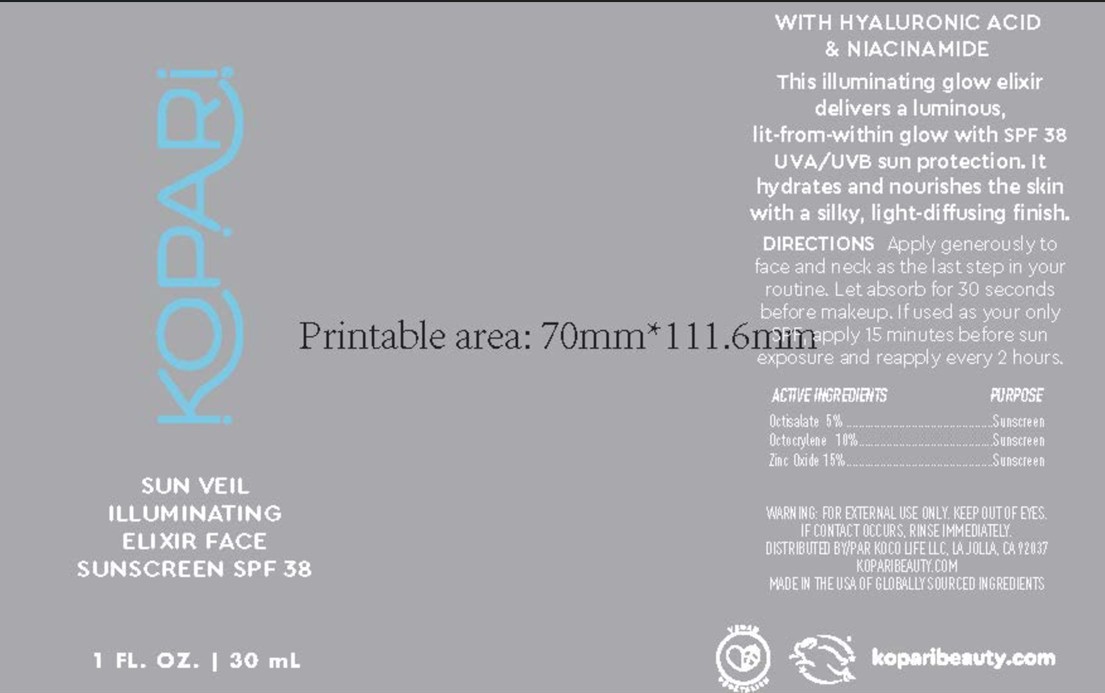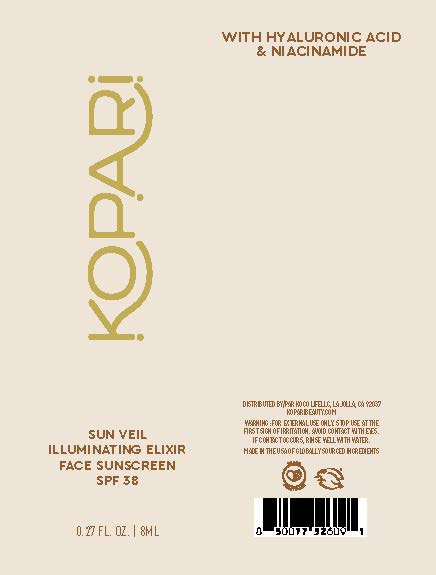 DRUG LABEL: Sun Veil IlluminatingElixir Face Sunscreen SPF 38
NDC: 84130-019 | Form: LOTION
Manufacturer: Koco Life LLC
Category: otc | Type: HUMAN OTC DRUG LABEL
Date: 20260205

ACTIVE INGREDIENTS: OCTISALATE 50 mg/1 mL; OCTOCRYLENE 100 mg/1 mL; ZINC OXIDE 150 mg/1 mL
INACTIVE INGREDIENTS: SODIUM FERROCYANIDE; ETHYLHEXYLGLYCERIN; POLYGLYCERYL-3 PENTARICINOLEATE; CI 77491; CI 77499; TITANIUM DIOXIDE; WATER; LIMONENE, (+)-; 1,2-HEXANEDIOL; 3,6-NONADIEN-1-OL, (3Z,6Z)-; CITRUS AURANTIUM PEEL OIL; SODIUM HYALURONATE; CITRUS AURANTIFOLIA (LIME) OIL; DIMETHYL HEPTENAL; HEXYL ACETATE; SODIUM CHLORIDE; MICA; TERPINEOL; LITSEA CUBEBA FRUIT OIL; SODIUM HYDROXIDE; ETHYL BUTYRATE; TIN OXIDE; TOCOPHEROL; MALTOL; CAPRYLIC/CAPRIC TRIGLYCERIDE; MENTHA VIRIDIS (SPEARMINT) LEAF OIL; GERANYL ACETATE; NIACINAMIDE; BENZYL ALCOHOL; FERRIC TITANATE; PANTHENOL; XANTHAN GUM; GAMMA-DECALACTONE; CITRUS AURANTIUM DULCIS (ORANGE) PEEL OIL; TRIETHYL CITRATE; BUTYLOCTYL SALICYLATE; GERANIOL; PROPANEDIOL

Sun Veil Illuminating Elixir Face Sunscreen SPF38

Active ingredients

Octisalate 5%

Octocrylene 10%

Zinc Oxide 15%

Purpose

Octisalate 5%.......................................Sunscreen

Octocrylene 10%..................................Sunscreen

Zinc Oxide 15%.....................................Sunscreen

Uses

• Helps prevent sunburn

• If used as directed with other sun protectionmeasures (see Directions), decreases the riskof skin cancer and early skin aging causedby the sun

Warnings

For external use only

Do not use on damaged or broken skin

When using this product keep out of eyes.
Rinse with water to remove

Stop use and ask a doctor if rash occurs

Keep out of reach of children. If product is swallowed, get medical help or contact a Poison Control Center right away

Directions

• Apply generously & evenly 15 minutes before sun exposure.

REAPPLY: • At least every 2 hours • Use a water resistant sunscreen if swimming or sweating. Sun Protection Measures: spending time in the sun increases your risk of skin cancer and early skin aging.To decrease this risk, regularly use a sunscreen with a Broad Spectrum SPF value of 15 or higher and other sun protection measures including: • Limit time in the sun, especially from 10 a.m.- 2 p.m. • Wearlong-sleeved shirts, pants, hats, and sunglasses.

• Children under 6 months: Ask doctor

Other information

Protect the product in this container from excessive heat and direct sun

Inactive ingredients

Water/Aqua/Eau, Butyloctyl Salicylate, Polyglyceryl-3 Polyricinoleate, Propanediol, Sodium Chloride, Caprylic/Capric Triglyceride, Mica, Niacinamide, Sodium Hyaluronate, Panthenol, Litsea Cubeba Fruit Oil, Citrus Aurantium Dulcis (Orange) Peel Oil, Mentha Viridis (Spearmint) Leaf Oil, Citrus Aurantifolia (Lime) Oil, Tocopherol, 1,2-Hexanediol, Styrene/MA Copolymer, Ethylhexylglycerin, Triethyl Citrate, Xanthan Gum, Maltol, Dimethyl Heptenal, Gamma-Decalactone, Geraniol, Geranyl Acetate, 3,6-Nonadienol, Terpineol, Hexyl Acetate, Ethyl Butyrate, Benzyl Alcohol, Limonene, Citrus Aurantium Peel Oil, Sodium Hydroxide, Tin Oxide,Sodium Ferrocyanide, Iron Titanium Oxide, Titanium Dioxide (CI 77891), Iron Oxides (CI 77491), Iron Oxides (CI 77499).

Questions or comments?

Call (858) 252-0099

PACKAGE LABEL

Kopari

Sun Veil Illuminating Elixir Face Sunscreen

SPF 38

1 Fl. Oz. | 30 mL